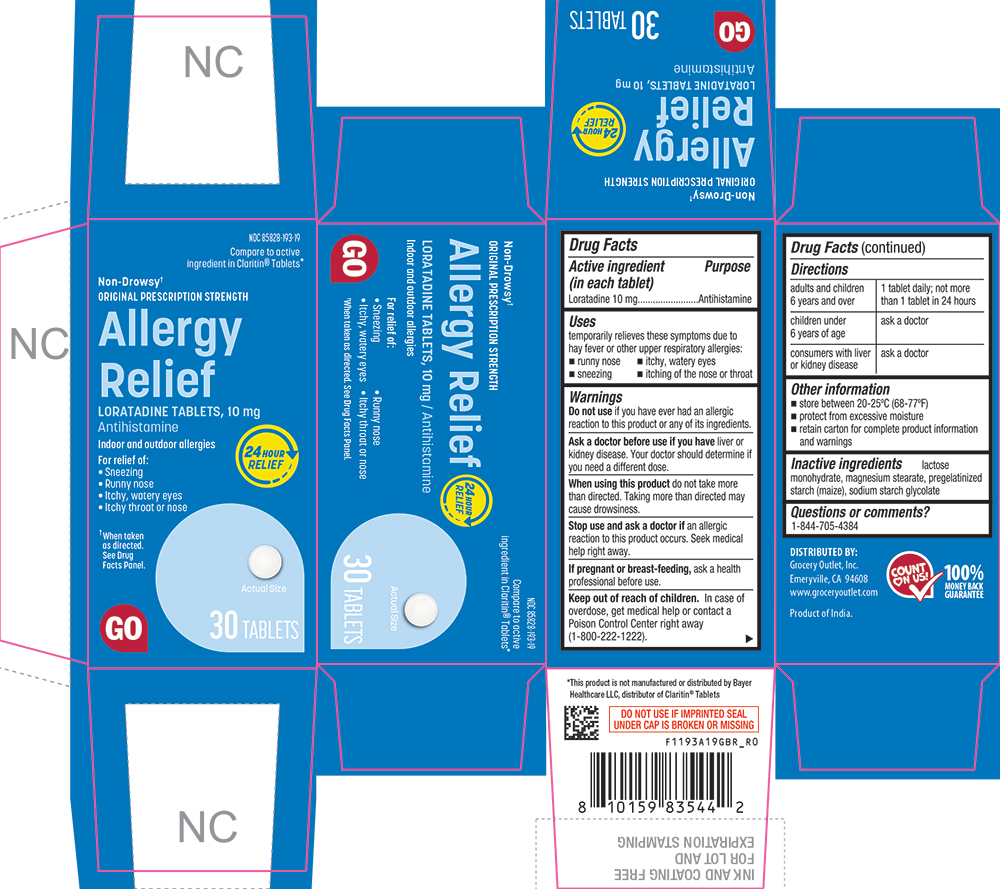 DRUG LABEL: Allergy Relief
NDC: 85828-193 | Form: TABLET
Manufacturer: Grocery Outlet, Inc
Category: otc | Type: HUMAN OTC DRUG LABEL
Date: 20260218

ACTIVE INGREDIENTS: LORATADINE 10 mg/1 1
INACTIVE INGREDIENTS: LACTOSE MONOHYDRATE; MAGNESIUM STEARATE; STARCH, CORN; SODIUM STARCH GLYCOLATE TYPE A POTATO

1193A-GBR-2026-0218

Drug Facts

Active ingredient (in each tablet)

Loratadine 10 mg

Purpose

Antihistamine

Uses

temporarily relieves these symptoms due to hay fever or other upper respiratory allergies:

- runny nose
- sneezing
- itchy, watery eyes
- itching of the nose or throat

Warnings

DO NOT USE

Do not useif you have ever had an allergic reaction to this product or any of its ingredients.

Ask a doctor before use if you haveliver or kidney disease. Your doctor should determine if you need a different dose.

WHEN USING

When using this productdo not take more than directed. Taking more than directed may cause drowsiness.

Stop use and ask a doctor if an allergic reaction to this product occurs. Seek medical help right away.

PREGNANCY OR BREAST FEEDING

If pregnant or breast-feeding, ask a health professional before use

Keep out of reach of children.

In case of overdose, get medical help or contact a Poison Control Center right away (1-800-222-1222).

Directions

adults and children 6 years and over | 1 tablet daily; not more than 1 tablet in 24 hours
children under 6 years of age | ask a doctor
consumers with liver or kidney disease | ask a doctor

Other information

- store between 20 to 25°C (68 to 77°F)
- retain carton for complete product information and warnings

Inactive ingredients

lactose monohydrate, magnesium stearate, pregelatinized starch (maize), sodium starch glycolate

Questions or comments?

1-844-705-4384

PRINCIPAL DISPLAY PANEL

NDC 85828-193-19

Compare to active ingredient in Claritin® Tablets*

Non-Drowsy†

ORIGINAL PRESCRIPTION STRENGTH

Allergy Relief

LORATADINE TABLETS, 10 mg

Antihistamine

Indoor and outdoor allergies

For relief of:

• Sneezing

• Runny nose

• Itchy, watery eyes

• Itchy throat or nose

†When taken as directed. See Drug Facts Panel.

GO

Actual Size

30 TABLETS